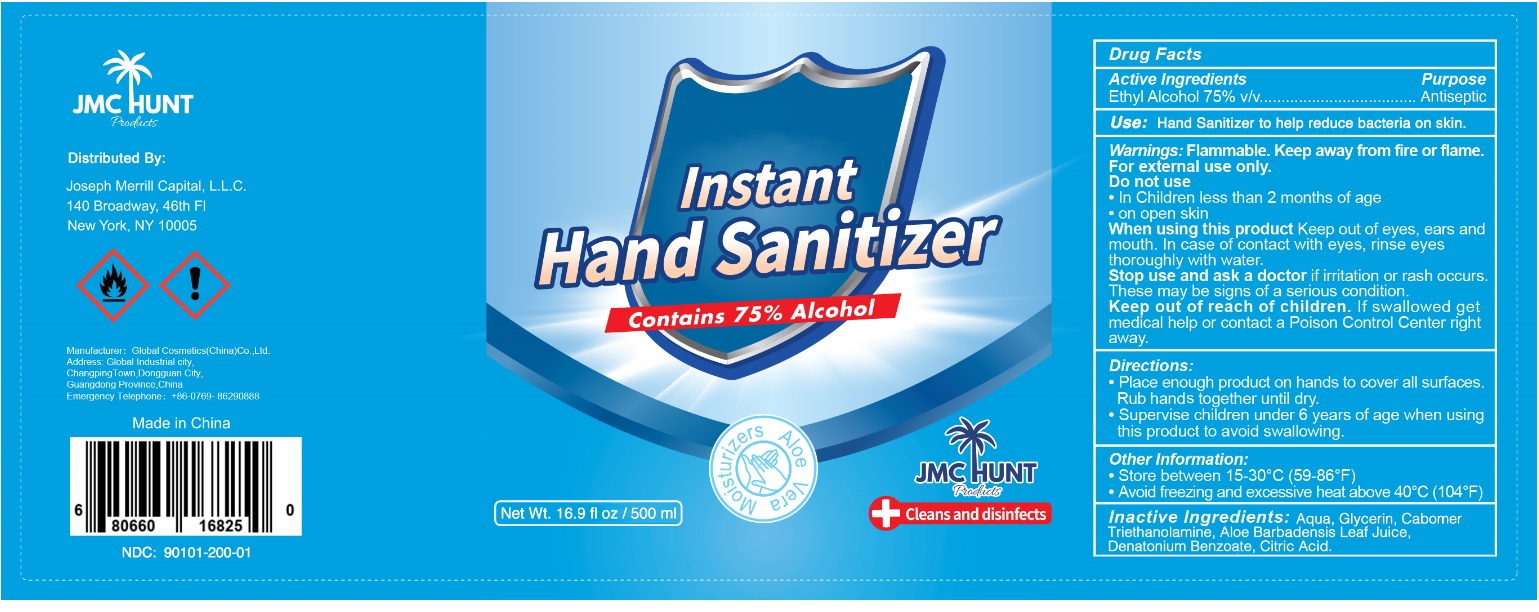 DRUG LABEL: JMC Hunt Instant Hand Sanitizer
NDC: 90101-200 | Form: GEL
Manufacturer: Joseph Merrill Capital Llc
Category: otc | Type: HUMAN OTC DRUG LABEL
Date: 20200806

ACTIVE INGREDIENTS: ALCOHOL 75 mL/100 mL
INACTIVE INGREDIENTS: WATER; GLYCERIN; CARBOMER HOMOPOLYMER, UNSPECIFIED TYPE; TROLAMINE; ALOE VERA LEAF; DENATONIUM BENZOATE; CITRIC ACID MONOHYDRATE

JMC HUNT Instant Hand Sanitizer

Active Ingredients

Ethyl Alcohol 75% v/v

Purpose

Antiseptic

INDICATIONS AND USAGE

Use: Hand Sanitizer to help reduce bacteria on skin.

Warnings: Flammable. Keep away from fire or flame.

For external use only.

Do not use

• In Children less than 2 months of age

• on open skin

When using this product Keep out of eyes, ears and mouth. In case of contact with eyes, rinse eyes thoroughly with water.

Stop use and ask a doctor if irritation or rash occurs. These may be signs of a serious condition.

Keep out of reach of children. If swallowed get medical help or contact a Poison Control Center right away.

Directions:

• Place enough product on hands to cover all surfaces. Rub hands together until dry.

• Supervise children under 6 years of age when using this product to avoid swallowing.

Other Information:

• Store between 15-30°C (59-86°F)

• Avoid freezing and excessive heat above 40°C (104°F)

INACTIVE INGREDIENT

Inactive ingredients: Aqua, Glycerin, Cabomer, Triethanolamine, Aloe Barbadensis Leaf Juice, Denatonium Benzoate, Citric Acid

Contains 75% Alcohol

Moisturizers

Aloe Vera

Cleans and disinfects

Distributed By:

Joseph Merrill Capital, L.L.C.

140 Broadway, 46th FI

New York, NY 10005

Manufacturer: Global Cosmetics(China)Co., Ltd.

Address: Global Industrial city,

Changping Town, Dongguan City,

Guangdong Province, China

Emergency Telephone: +86-0769- 8629088

Made in China